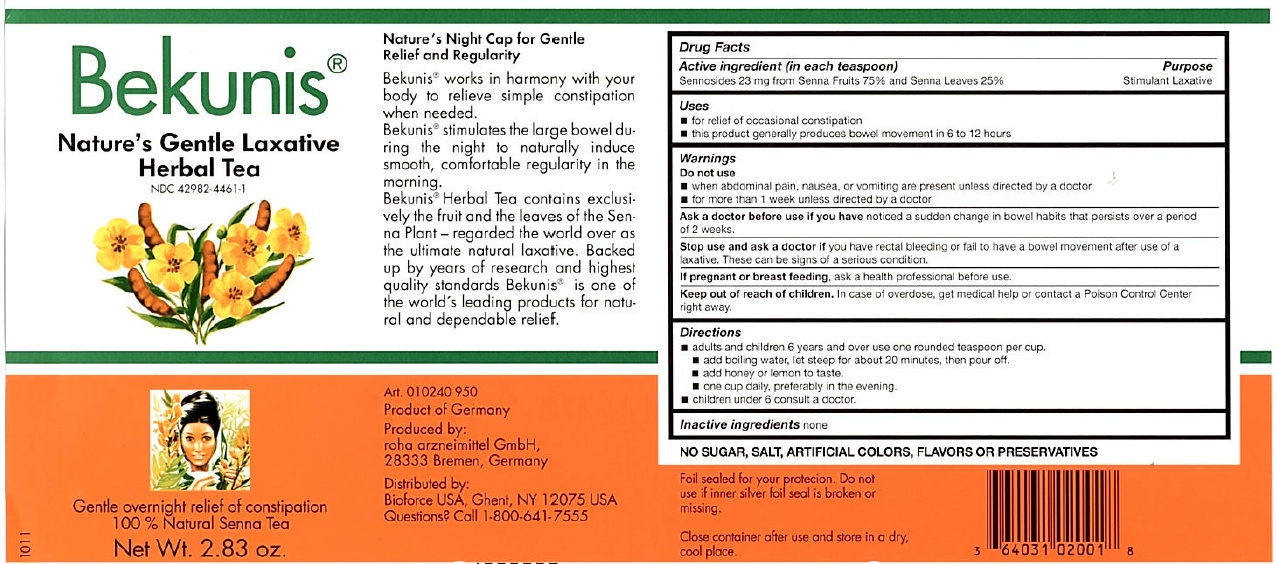 DRUG LABEL: Bekunis Natures Gentle Laxative Herbal Tea
NDC: 42982-4461 | Form: EXTRACT
Manufacturer: roha arzneimittel GmbH
Category: otc | Type: HUMAN OTC DRUG LABEL
Date: 20110324

ACTIVE INGREDIENTS: SENNOSIDES A AND B 23 mg/1 g

Bekunis Nature's Gentle Laxative Herbal Tea

Active Ingredient (in each teaspoon)

Sennosides 23mg from Senna Fruits 75% and Senna Leaves 75%

Purpose

Stimulant laxative

Uses

For relief of occasional constipation

this product generally produces bowel movement in 6 to 12 hours.

Warnings

do not use when abdominal pain, nausea, or vomiting are present unless directed by a doctor

for more than 1 week unless directed by a doctor.

Ask a doctor before use

if you have noticed a sudden change in bowel habits that persists over a period of 2 weeks.

Stop use and ask a doctor if

you have rectal bleeding or fail to have a bowel movement after use of a laxative. These can be signs of a serious condition.

If pregnant of breast feeding

Ask a health professional before use.

Keep out of reach of children.

In case of overdose, get medical help or contact a Poison Control Center right away.

Directions

adults and children 6 years and over use one rounded teaspoon per cup.

add cold or lukewarm water, stir.

add honey or lemon to taste.

one cup daily, prefrably in the evening

Children under 6 consult a doctor

Inactive Ingredients

none.

Nature's Night Cap for Gentle Relief and Regularity

Bekunis works in harmony with your body to relieve simple constipation when needed. Bekunis stimulates the large bowel during the night to naturally induce smooth, comfortable regularity in the morning. Bekunis Instant Tea is made exclusively from the fruit of the Senna Plant - regarded the world over as the ultimate natural laxative. backed up by years of research and highest quality standards. Bekunis is one of the worlds leading products for natural and dependable relief.

Foil sealed for your protection. Do not use if inner silver foil seal is broken or missing.

Close container after use and store in a dry, cool place.

Gentle overnight relief of constipation 100% Natural Senna Tea

PACKAGE LABEL

Bekunis

Nature's Gentle Laxative

Herbal Tea

NDC 42982-4451-2

Gentle overnight relief of constipation

100% Natural Senna Tea

Net Wt. 2.83 oz

Produced in Germany

roha arzneimittel GmbH

28333 Bremen, Germany

Distributed by Bioforce USA,

Ghent, NY 12075 USA

Questions Call 1-800-641-7555